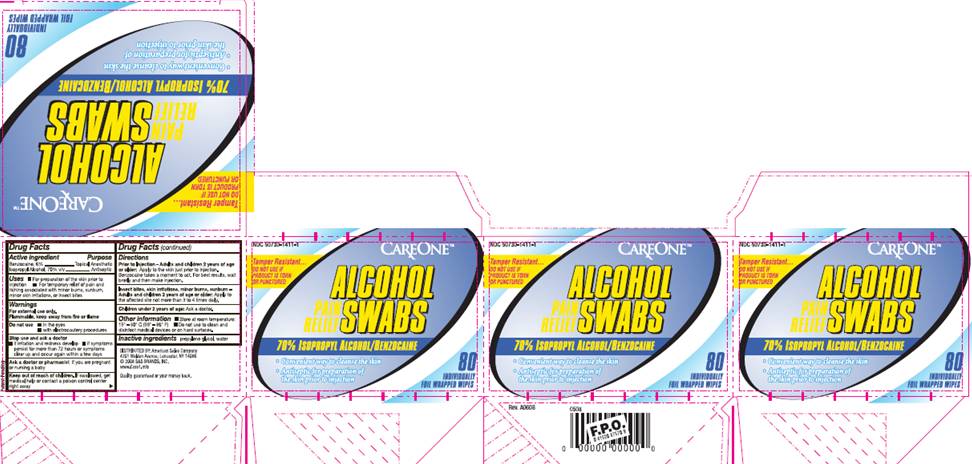 DRUG LABEL: Alcohol Prep Pad with Benzocaine
NDC: 50730-1411 | Form: SWAB
Manufacturer: H and P Industries, Inc. dba Triad Group
Category: otc | Type: HUMAN OTC DRUG LABEL
Date: 20091211

ACTIVE INGREDIENTS: benzocaine .06 mL/1 1; isopropyl alcohol .70 mL/1 1
INACTIVE INGREDIENTS: propylene glycol; water

DRUG FACTS

ACTIVE INGREDIENTS

Benzocaine 6%
Isopropyl alcohol 70% v/v

PURPOSE

Topical Anesthetic

Antiseptic

USES

- For preparation of the skin prior to injection
- For temporary relief of pain and itching associated with minor burns, sunburn, minor skin irritations, or insect bites

WARNINGS

For external use only.
Flammable, keep away from fire or flame.

Do not use

- in the eyes
- with electrocautery procedures

Stop use and ask a doctor

- if irritation and redness develop
- if symptoms persist for more than 72 hours or symptoms clear up and occur within a few days.

Ask a doctor or pharmacist

if you are pregnant or nursing a baby.

Keep out of reach of children

If swallowed, get medical help or contact a Poison Control Center right away.

DIRECTIONS

Prior to Injection - Adults and children 2 years of age or older:
Apply to the skin just prior to injection. Benzocaine takes a minute to act. for best results, wait briefly and then make injection.
Insect bites, skin irritations, minor burns, sunburn -
Adults and children 2 years of age or older:
Apply to the affected site not more than 3 to 4 times daily.
Children under 2 years of age: Ask a doctor.

STORAGE AND HANDLING

- Store at room temperature: 15° - 30° C (59° - 86° F)
- Do not use to clean and disinfect medical devices or hard surfaces.

INACTIVE INGREDIENTS

propylene glycol, purified water

CARTON INFORMATION

NDC 50730-1411-1

Tamper Resistant. . . .do not use if product is torn or punctured

CAREONE

ALCOHOL
Pain Relief SWABS

70% ISOPROPYL ALCOHOL/BENZOCAINE

- Convenient way to cleanse the skin
- Antiseptic for preparation of the skin prior to injection

80 Individually Foil Wrapped Wipes
DIST. BY: American Sales Company
4201 Walden Avenue, Lancaster, NY 14086
©2008 S and S BRANDS, INC.
www.Care1.info

Quality Guaranteed or your money back.